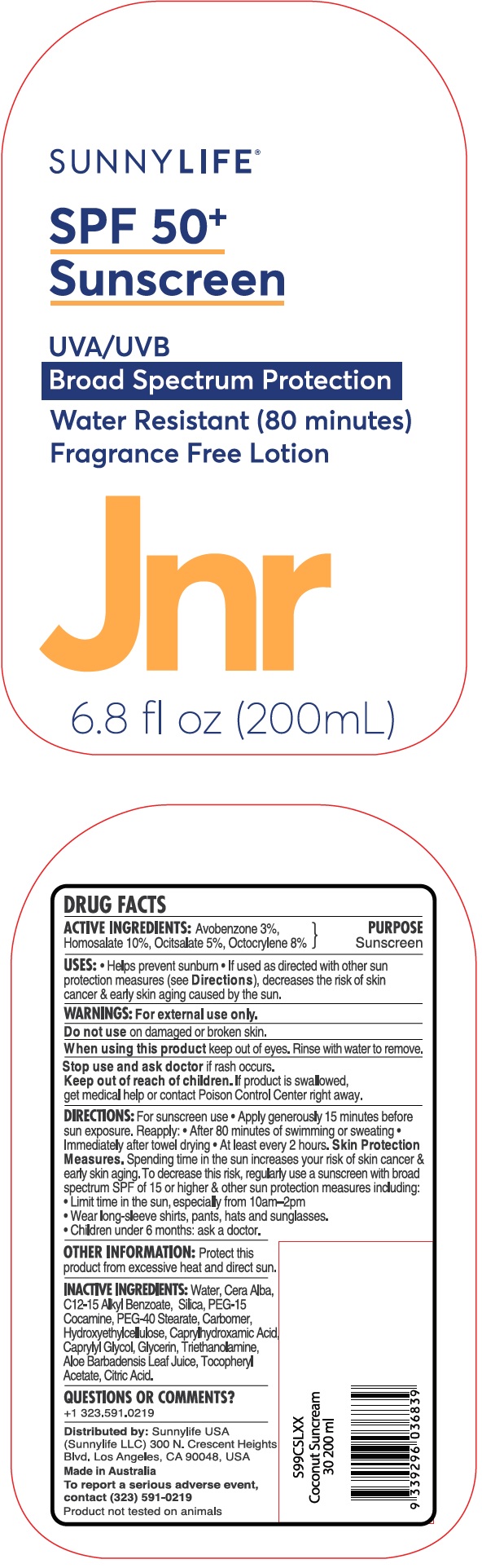 DRUG LABEL: SUNNYLIFE SPF 50 SUNSCREEN FRAGRANCE FREE
NDC: 72566-050 | Form: LOTION
Manufacturer: OUTLIVING PTY LTD
Category: otc | Type: HUMAN OTC DRUG LABEL
Date: 20181108

ACTIVE INGREDIENTS: AVOBENZONE 30 mg/1 mL; HOMOSALATE 100 mg/1 mL; OCTISALATE 50 mg/1 mL; OCTOCRYLENE 80 mg/1 mL
INACTIVE INGREDIENTS: WATER; WHITE WAX; ALKYL (C12-15) BENZOATE; SILICON DIOXIDE; PEG-15 COCAMINE; PEG-40 STEARATE; CARBOXYPOLYMETHYLENE; CAPRYLHYDROXAMIC ACID; CAPRYLYL GLYCOL; GLYCERIN; TROLAMINE; ALOE VERA LEAF; CITRIC ACID MONOHYDRATE

SUNNYLIFE SPF 50+ SUNSCREEN FRAGRANCE FREE LOTION JNR

ACTIVE INGREDIENTS:

Avobenzone 3%, Homosalate 10%

Ocitsalate 5% Octocrylene 8%

PURPOSE

Sunscreen

Uses:

- Helps prevent sunburn
- If used as directed with other sun protection measures (see Directions), decreases the risk of skin cancer & early skin aging caused by the sun.

WARNINGS:

For external use only.

Do not use

on damaged or broken skin.

When using this product

keep out of eyes. Rinse with water to remove.

Stop use and ask doctor

if rash occurs.

Keep out of reach of children.

If product is swallowed, get medical help contact Poison Control Center right away.

DIRECTION:

- For sunscreen use
- Apply generously 15 minutes before sun exposure. Reapply:
- After 80 minutes of swimming or sweating
- Immediately after towel drying
- At least every 2 hours. Skin Protection Measures. Spending time in the sun increases your risk of skin cancer & early sking aging. To decrease this risk, regularly use a sunscreen with broad spectrum SPF of 15 or higher & other sun protection measures including:
- Limit time in the sun, especially from 10am-2pm
- Wear long-sleeve shirts, pants, hats and sunglasses.
- Children under 6 months: ask a doctor.

OTHER INFORMATION:

Protect this product from excessive heat and direct sun.

INACTIVE INGREDIENTS:

Water, Cera Alba, C12-15 Alkyl Benzoate, SIlica, PEG-15 Cocamine, PEG-40 Stearate, Carbomer, Hydroxyethylcellulose, Caprylhydroxamic Acid, Caprylyl Glycol, Glycerin, Triethanolamine, Aloe Barbadensis Leaf Juice, Tocopheryl Acetate, Citric Acid.

QUESTIONS OR COMMENTS?

+1 323.591.0219